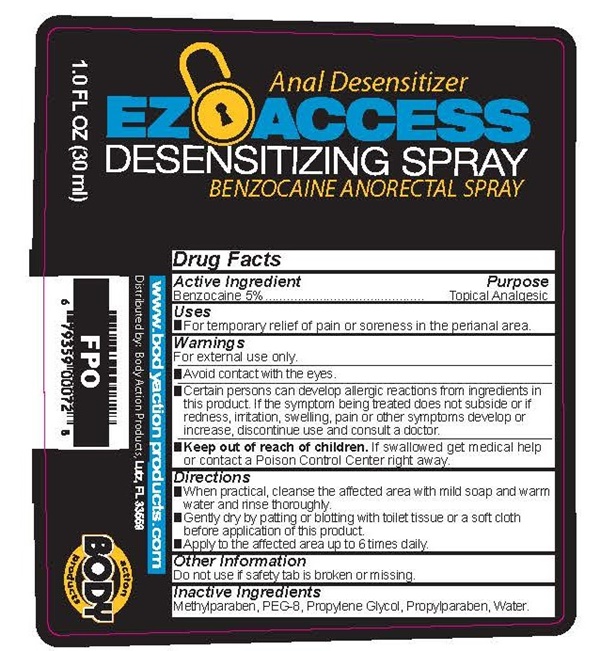 DRUG LABEL: EZ ACCESS
NDC: 70742-001 | Form: LIQUID
Manufacturer: Product Max Group Inc
Category: otc | Type: HUMAN OTC DRUG LABEL
Date: 20160805

ACTIVE INGREDIENTS: BENZOCAINE 1417 mg/30 mL
INACTIVE INGREDIENTS: METHYLPARABEN; POLYETHYLENE GLYCOL 400; PROPYLENE GLYCOL; PROPYLPARABEN; WATER

EZ ACCESS - 001

Drug Facts Active Ingredient

Benzocaine 5%

Purpose

Topical Analgesic

- Keep out of reach of children. If swallowed get medical help or contact a Poison Control Center right away.

Uses

- For temporary relief of pain or soreness in the perianal area.

Warnings

For external use only.

- Avoid contact with the eyes.
- Certain persons can develop allergic reactions from ingredients in this product. If the symptom being treated does not subside or if redness, irritation, swelling, pain or other symptoms develop or increase, discontinue use a consult a doctor.

Directions

- When practical, cleanse the affected area with mild soap and water and rinse thoroughly.
- Gently dry by patting or blotting with a tissue or a soft cloth before the application of this product.
- Apply to the affected area up to 6 times daily.

Other information

Do not use if safety tab is broken or missing

Inactive Ingredients

Methylparaben, PEG-8, Propylene Glycol, Propylparaben, Water

EZ ACCESS product label

Anal Desensitizer

EZ ACCESS

DESENSITIZING SPRAY
BENZOCAINE ANORECTAL SPRAY

1.0 FL OZ (30mL)

www.bodyactionproducts.com

Distributed by: BodyAction Products, Lutz, FL 33559

action BODY products